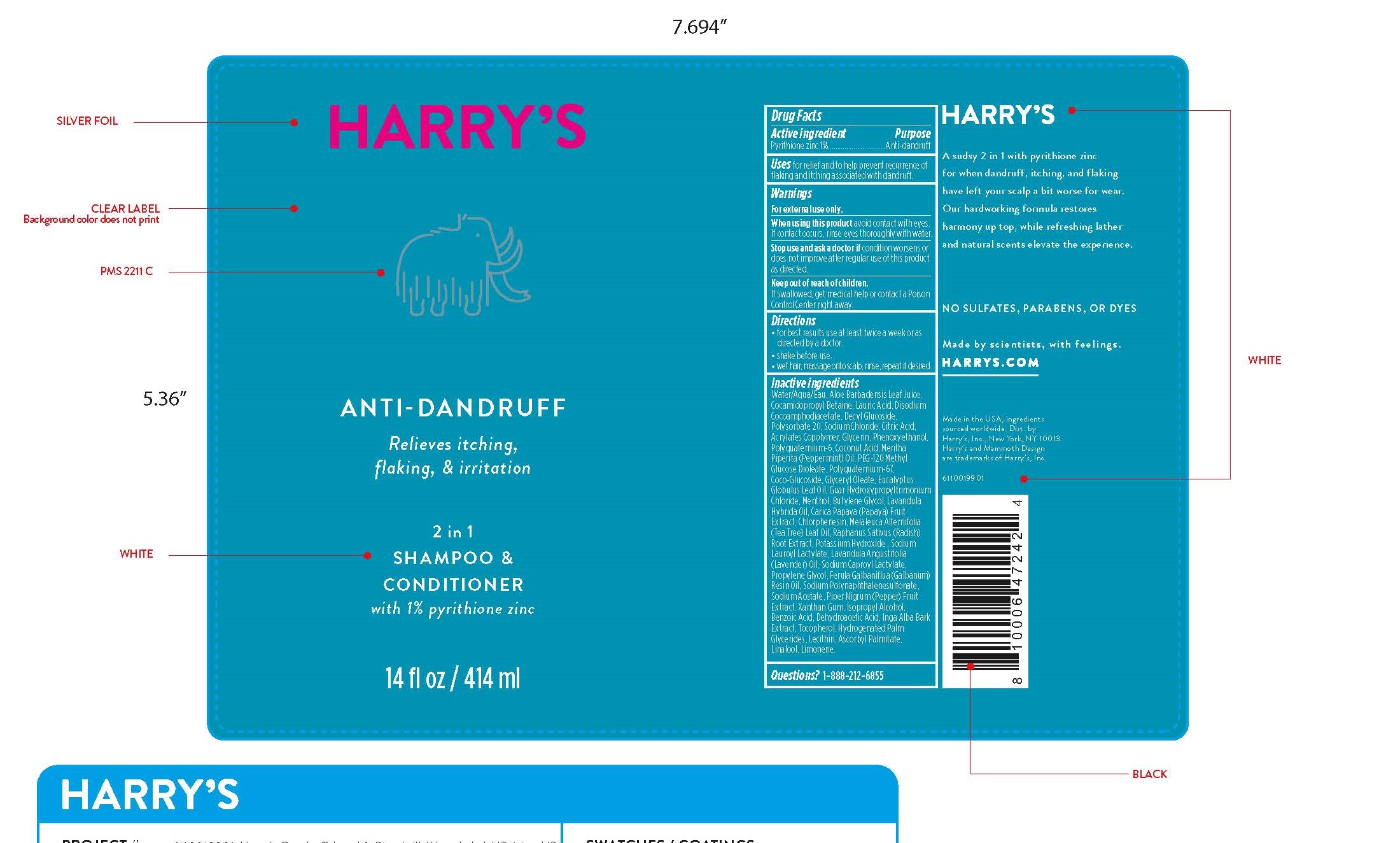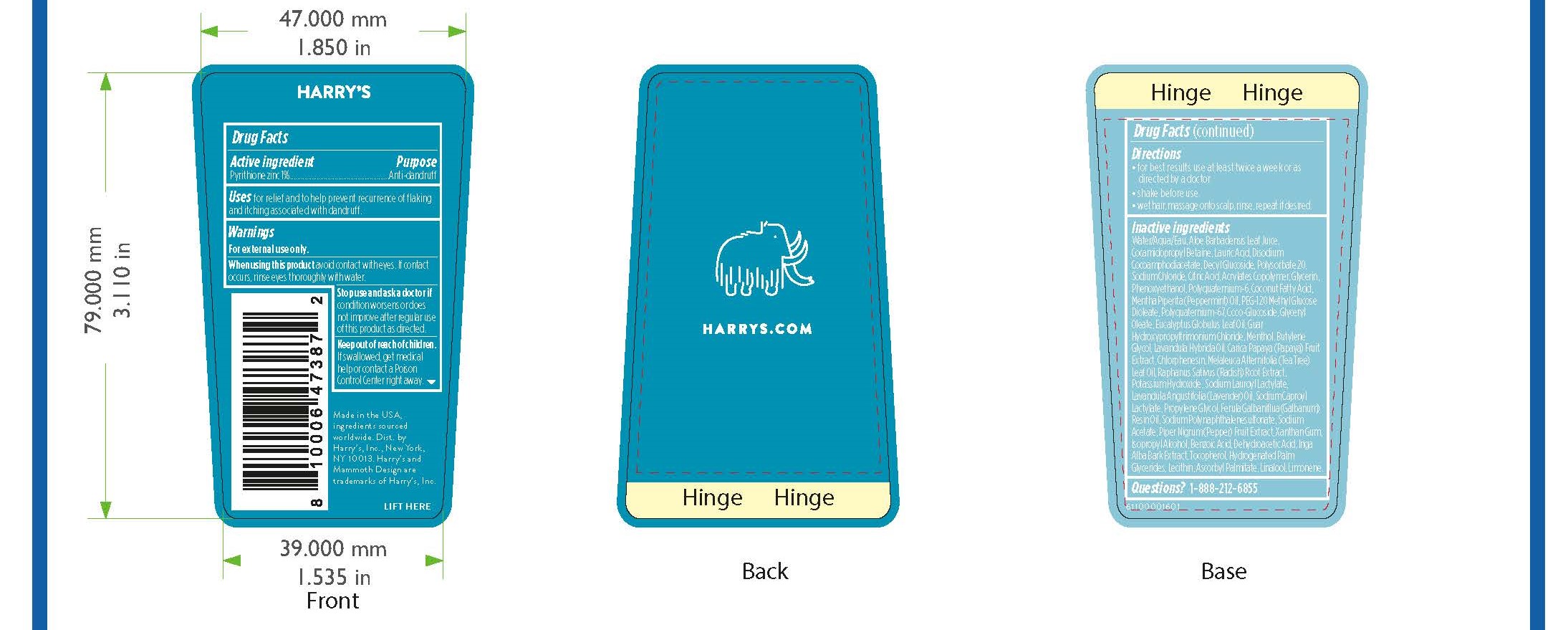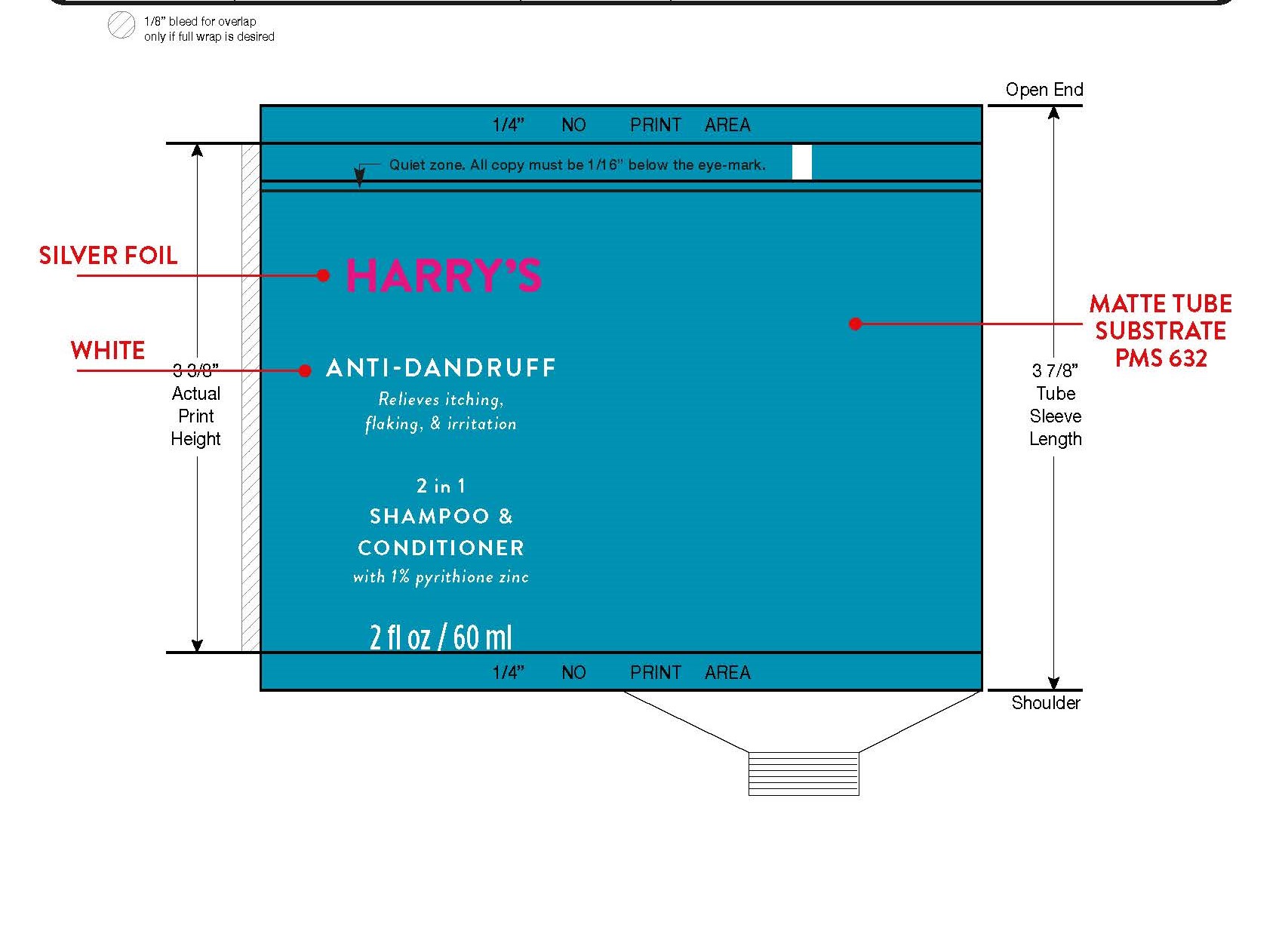 DRUG LABEL: Zinc Pyrithione
NDC: 70533-003 | Form: SHAMPOO
Manufacturer: Harry's Inc.
Category: otc | Type: HUMAN OTC DRUG LABEL
Date: 20241216

ACTIVE INGREDIENTS: PYRITHIONE ZINC 10 mg/1 mL
INACTIVE INGREDIENTS: DECYL GLUCOSIDE; POLYQUATERNIUM-6 (15000 MW); PROPYLENE GLYCOL; LIMONENE, (+/-)-; FORMALDEHYDE/SODIUM NAPHTHALENESULFONATE COPOLYMER (3000 MW); ALOE; COCAMIDOPROPYL BETAINE; PAPAYA; LAURIC ACID; INGA ALBA BARK; TOCOPHEROL; LECITHIN, SUNFLOWER; POLYQUATERNIUM-10 (400 CPS AT 2%); SODIUM CHLORIDE; ANHYDROUS CITRIC ACID; BUTYLENE GLYCOL; LAVANDIN OIL; PHENOXYETHANOL; COCO GLUCOSIDE; GUAR HYDROXYPROPYLTRIMONIUM CHLORIDE (1.7 SUBSTITUENTS PER SACCHARIDE); RACEMENTHOL; CHLORPHENESIN; TEA TREE OIL; GALBANUM OIL; DEHYDROACETIC ACID; METHACRYLIC ACID - ETHYL ACRYLATE COPOLYMER (4500 MPA.S); GLYCERYL OLEATE; EUCALYPTUS OIL; LINALOOL, (+/-)-; SODIUM ACETATE ANHYDROUS; WHITE PEPPER; RAPHANUS SATIVUS VAR. CAUDATUS ROOT; HYDROGENATED PALM GLYCERIDES; COCONUT ACID; PEPPERMINT OIL; ASCORBYL PALMITATE; XANTHAN GUM; BENZOIC ACID; POTASSIUM HYDROXIDE; LAVENDER OIL; SODIUM CAPROYL LACTYLATE; PEG-120 METHYL GLUCOSE DIOLEATE; ISOPROPYL ALCOHOL; WATER; DISODIUM COCOAMPHODIACETATE; POLYSORBATE 20; GLYCERIN; SODIUM LAUROYL LACTYLATE

Anti-dandruff

Active ingredient

Pyrithione zinc 1%

Purpose

Anti-dandruff

Uses

for relief and to help prevent recurrence of
flaking and itching associated with dandruff.

Warnings

For external use only.

When using this product avoid contact with eyes. If contact occurs, rinse eyes thoroughly with water

Stop use and ask a doctor if condition worsens or does not improve after regular use of this product as directed.

Keep out of reach of children. If swallowed, get medical help or contact a Poison Control Center right away.

Directions

• for best results use at least twice a week or as
directed by a doctor.
• shake before use.
• wet hair, massage onto scalp, rinse, repeat if desired.

Inactive ingredients

Water/Aqua/Eau, Aloe Barbadensis Leaf Juice, Cocamidopropyl Betaine, Lauric Acid, Disodium Cocoamphodiacetate, Decyl Glucoside, Polysorbate 20, Sodium Chloride, Citric Acid, Acrylates Copolymer, Glycerin, Phenoxyethanol, Polyquaternium-6, Coconut Acid, Mentha Piperita (Peppermint) Oil, PEG-120 Methyl Glucose Dioleate, Polyquaternium-67, Coco-Glucoside, Glyceryl Oleate, Eucalyptus Globulus Leaf Oil, Guar Hydroxypropyltrimonium Chloride, Menthol, Butylene Glycol, Lavandula Hybrida Oil, Carica Papaya (Papaya) Fruit Extract, Chlorphenesin, Melaleuca Alternifolia (Tea Tree) Leaf Oil, Raphanus Sativus (Radish)
Root Extract, Potassium Hydroxide , Sodium Lauroyl Lactylate, Lavandula Angustifolia (Lavender) Oil, Sodium Caproyl Lactylate,
Propylene Glycol, Ferula Galbaniflua (Galbanum) Resin Oil, Sodium Polynaphthalenesulfonate, Sodium Acetate, Piper Nigrum (Pepper) Fruit Extract, Xanthan Gum, Isopropyl Alcohol, Benzoic Acid, Dehydroacetic Acid, Inga Alba Bark Extract, Tocopherol, Hydrogenated Palm Glycerides, Lecithin, Ascorbyl Palmitate, Linalool, Limonene.

Questions? 1-888-212-6855

PACKAGE LABEL

414ml NDC: 70533-003-14

59ml NDC: 70533-003-02